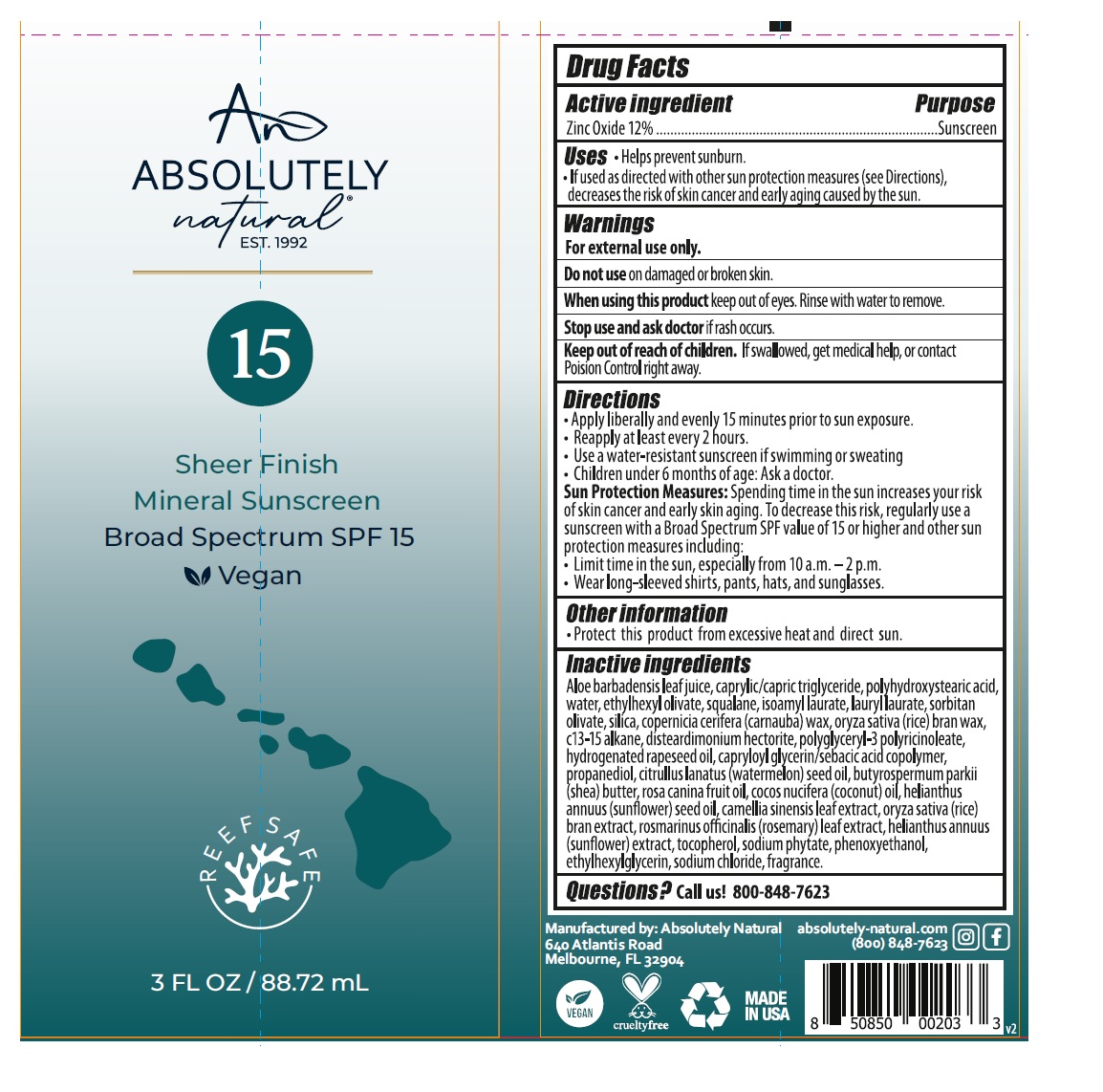 DRUG LABEL: Absolutely Natural Broad Spectrum SPF 15 Sunscreen
NDC: 70793-037 | Form: LOTION
Manufacturer: Absolutely Natural
Category: otc | Type: HUMAN OTC DRUG LABEL
Date: 20241213

ACTIVE INGREDIENTS: ZINC OXIDE 12 g/100 mL
INACTIVE INGREDIENTS: ALOE VERA LEAF; MEDIUM-CHAIN TRIGLYCERIDES; POLYHYDROXYSTEARIC ACID (2300 MW); WATER; ETHYLHEXYL OLEATE; SQUALANE; ISOAMYL LAURATE; LAURYL LAURATE; SORBITAN OLIVATE; SILICON DIOXIDE; CARNAUBA WAX; RICE BRAN; C13-15 ALKANE; DISTEARDIMONIUM HECTORITE; POLYGLYCERYL-3 PENTARICINOLEATE; HYDROGENATED RAPESEED OIL; CAPRYLOYL GLYCERIN/SEBACIC ACID COPOLYMER (2000 MPA.S); PROPANEDIOL; WATERMELON SEED OIL; SHEA BUTTER; ROSA CANINA FRUIT OIL; COCONUT OIL; SUNFLOWER OIL; GREEN TEA LEAF; ROSEMARY; HELIANTHUS ANNUUS FLOWERING TOP; TOCOPHEROL; PHYTATE SODIUM; PHENOXYETHANOL; ETHYLHEXYLGLYCERIN; SODIUM CHLORIDE

ABSOLUTELY natural® Broad Spectrum SPF 15 Mineral Sunscreen

Active ingredient

Zinc Oxide 12%

Purpose

Sunscreen

Uses

• Helps prevent sunburn.
• If used as directed with other sun protection measures (see Directions), decreases the risk of skin cancer and early aging caused by the sun.

Warnings

For external use only.

Do not use on damaged or broken skin.

When using this product keep out of eyes. Rinse with water to remove.

Stop use and ask doctor if rash occurs.

Keep out of reach of children. If swallowed, get medical help, or contact Poison Control right away.

Directions

• Apply liberally and evenly 15 minutes prior to sun exposure.
• Reapply at least every 2 hours.
• Use a water-resistant sunscreen if swimming or sweating
• Children under 6 months of age: Ask a doctor.
Sun Protection Measures: Spending time in the sun increases your risk of skin cancer and early skin aging. To decrease this risk, regularly use a sunscreen with a Broad Spectrum SPF value of 15 or higher and other sun protection measures including:
• Limit time in the sun, especially from 10 a.m. - 2 p.m.
• Wear long-sleeved shirts, pants, hats, and sunglasses.

Other information

• Protect this product from excessive heat and direct sun.

Inactive ingredients

Aloe barbadensis leaf juice, caprylic/capric triglyceride, polyhydroxystearic acid, water, ethylhexyl olivate, squalane, isoamyl laurate, lauryl laurate, sorbitan olivate, silica, copernicia cerifera (carnauba) wax, oryza sativa (rice) bran wax, c13-15 alkane, disteardimonium hectorite, polyglyceryl-3 polyricinoleate, hydrogenated rapeseed oil, capryloyl glycerin/sebacic acid copolymer, propanediol, citrullus lanatus (watermelon) seed oil, butyrospermum parkii (shea) butter, rosa canina fruit oil, cocos nucifera (coconut) oil, helianthus annuus (sunflower) seed oil, camellia sinensis leaf extract, oryza sativa (rice) bran extract, rosmarinus officinalis (rosemary) leaf extract, helianthus annuus (sunflower) extract, tocopherol, sodium phytate, phenoxyethanol, ethylhexylglycerin, sodium chloride, fragrance.

Questions?

Call us! 800-848-7623

Sheer Finish

Mineral Sunscreen

Vegan

REEF SAFE

Manufactured by: Absolutely Natural
640 Atlantis Road
Melbourne, FL 32904

absolutely-natural.com
(800)-848-7623

crueltyfree

MADE IN USA